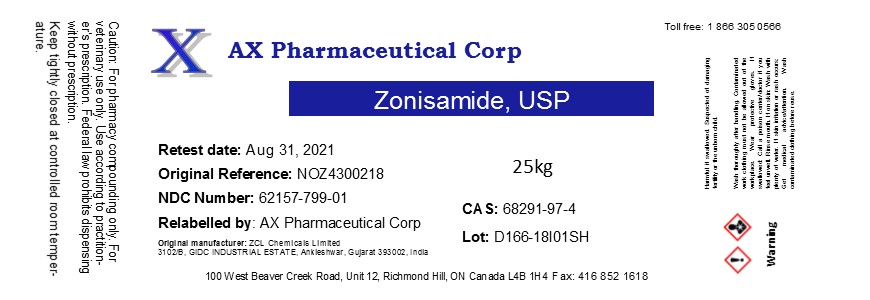 DRUG LABEL: Zonisamide
NDC: 62157-799 | Form: POWDER
Manufacturer: AX Pharmaceutical Corp
Category: other | Type: BULK INGREDIENT
Date: 20190322

ACTIVE INGREDIENTS: ZONISAMIDE 1 kg/1 kg

Zonisamide